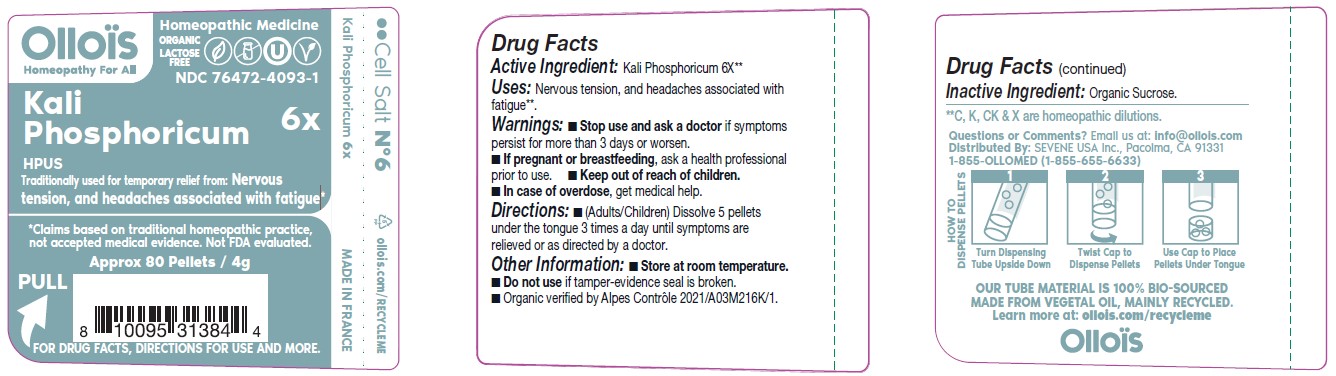 DRUG LABEL: KALI PHOSPHORICUM

NDC: 76472-4093 | Form: PELLET
Manufacturer: SEVENE USA
Category: homeopathic | Type: HUMAN OTC DRUG LABEL
Date: 20250211

ACTIVE INGREDIENTS: DIBASIC POTASSIUM PHOSPHATE 6 [hp_X]/1 1
INACTIVE INGREDIENTS: SUCROSE

SEVENE USA (as PLD) - KALI PHOSPHORICUM 6X (76472-4093)

ACTIVE INGREDIENT:

KALI PHOSPHORICUM 6X**

**C, K, CK & X are homeopathic dilutions.

Traditionally used for temporary relief from:

Nervous tension, and headaches associated with fatigue*

*Claims based on traditional homeopathic practice, not accepted medical evidence. Not FDA evaluated.

DIRECTIONS:

- (adults/children) Dissolve 5 pellets under the tongue three times a day until symptoms are relieved or as directed by a doctor.

USES:

Nervous tension, and headaches associated with fatigue*.

WARNINGS:

- Stop use and ask a doctor if symptoms persist for more than 3 days or worsen.

PREGNANCY OR BREAST FEEDING

- If pregnant or breast-feeding, ask a health professional before use.

- Keep out of reach of children.
- In case of overdose, get medical help.

OTHER INFORMATION:

- Store at room temperature.
- Do not use if tamper-evidence seal is broken.
- Organic verified by Alpes Control 2021/A03M216K/1.

INACTIVE INGREDIENT:

ORGANIC SUCROSE

QUESTIONS OR COMMENTS?

Email us at: info@ollois.com